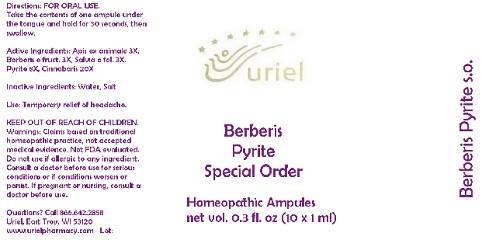 DRUG LABEL: Berberis Pyrite Special Order
NDC: 48951-2052 | Form: LIQUID
Manufacturer: Uriel Pharmacy Inc.
Category: homeopathic | Type: HUMAN OTC DRUG LABEL
Date: 20180521

ACTIVE INGREDIENTS: APIS MELLIFERA 3 [hp_X]/1 mL; BERBERIS VULGARIS ROOT BARK 3 [hp_X]/1 mL; SAGE 3 [hp_X]/1 mL; FERROUS DISULFIDE 8 [hp_X]/1 mL; MERCURIC SULFIDE 20 [hp_X]/1 mL
INACTIVE INGREDIENTS: WATER; SODIUM CHLORIDE

Berberis Pyrite Special Order

INDICATIONS AND USAGE

Directions: FOR ORAL USE.

DOSAGE AND ADMINISTRATION

Take the contents of one ampule under the tongue and hold for 30 seconds, then swallow.

ACTIVE INGREDIENT

Active Ingredients: Apis ex animale 3X, Berberis e fruct. 3X, Salvia e fol. 3X, Pyrite 8X, Cinnabaris 20X

Inactive Ingredients: Water, Salt

PURPOSE

Use: Temporary relief of headache.

KEEP OUT OF REACH OF CHILDREN.

WARNINGS

Warnings: Claims based on traditional homeopathic practice, not accepted medical evidence. Not FDA evaluated. Do not use if allergic to any ingredient. Consult a doctor before use for serious conditions or if conditions worsen or persist. If pregnant or nursing, consult a doctor before use.

QUESTIONS

Questions? Call 866.642.2858 Uriel, East Troy, WI 53120 www.urielpharmacy.com